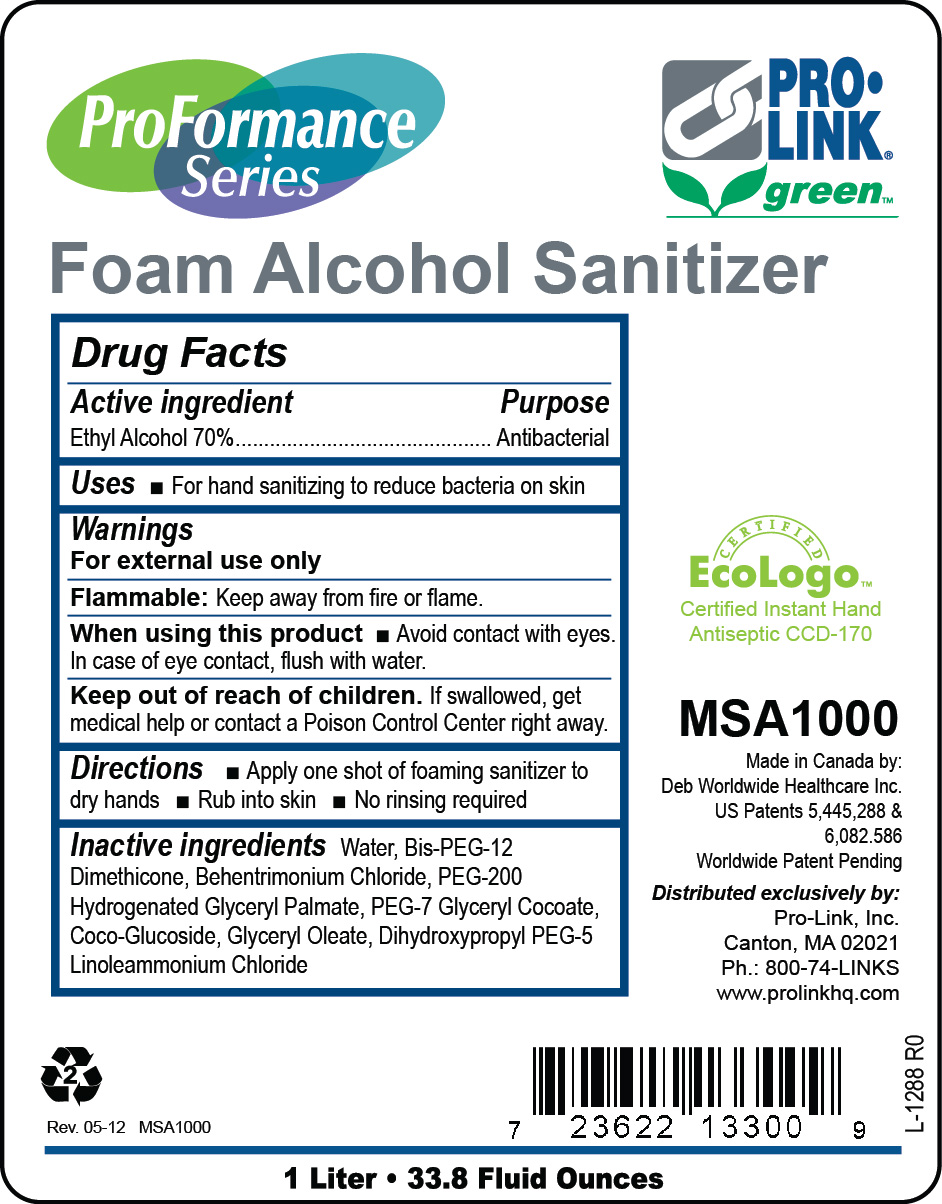 DRUG LABEL: Proformance Foam Alcohol Sanitizer
NDC: 66908-700 | Form: LIQUID
Manufacturer: Pro-Link, Inc.
Category: otc | Type: HUMAN OTC DRUG LABEL
Date: 20120509

ACTIVE INGREDIENTS: Alcohol 70 mL/100 mL
INACTIVE INGREDIENTS: WATER; DIHYDROXYPROPYL PEG-5 LINOLEAMMONIUM CHLORIDE; BEHENTRIMONIUM CHLORIDE; DIMETHICONE; COCO GLUCOSIDE; PEG-200 DILAURATE; GLYCERYL COCOATE; GLYCERYL MONOOLEATE

Drug Facts

Active ingredient

Ethyl Alcohol 70%

Purpose

Antibacterial

Uses

For hand sanitizing to reduce bacteria on the skin

Warnings

For external use only

Flammable: Keep away from fire or flame.

When using this product avoid contact with eyes. In case of eye contact, flush with water.

Keep out of reach of children.

If swallowed, get medical help or contact a Poison Control Center right away.

Directions

Apply one shot of foaming sanitizer to dry hands

Rub into skin

No rinsing required

Inactive ingredients

Water, Bis-PEG-12 Dimethicone, Behentrimonium Chloride, PEG-200 Hydrogenated Glyceryl Palmate, PEG-7 Glyceryl Cocoate, Coco-Glucoside, Glyceryl Oleate, Dihydroxypropyl PEG-5 Linoleammonium Chlroide

PACKAGE LABEL

ProFormance Series
Foam Alcohol Sanitizer
Pro Link green
Certified Ecologo
Certified Instant Hand Antiseptic CCD-170
MSA1000
Made in Canada by:
Deb Worldwide Healthcare Inc.
US Patents 5,445,288 and 6,082,586
Worldwide Patent Pending
Distributed exclusively by:
Pro-Link, Inc.
Canton, MA 02021
Ph.: 800-74-LINKS
www.prolinkhq.com
Rev. 05-12 MSA1000
1 Liter
33.8 Fluid Ounces